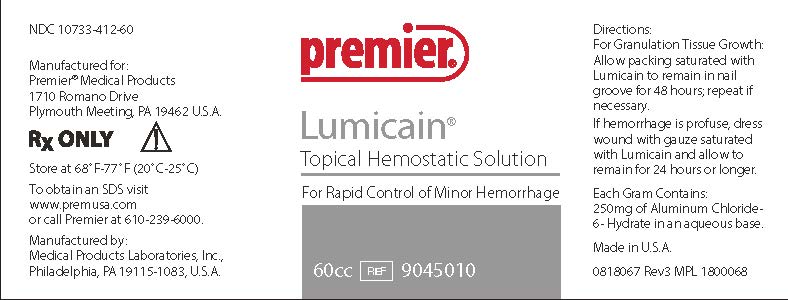 DRUG LABEL: lumicain
NDC: 10733-412 | Form: SOLUTION
Manufacturer: Medical Products Laboratories, Inc.
Category: prescription | Type: HUMAN PRESCRIPTION DRUG LABEL
Date: 20201223

ACTIVE INGREDIENTS: ALUMINUM CHLORIDE 250 mg/1 g
INACTIVE INGREDIENTS: WATER

lumicain Topical Hemostatic Solution

DOSAGE AND ADMINISTRATION

FOR TOPICAL APPLICATION ONLY

For Granulation Tissue Growth: Allow packing saturated in Lumicain to remain in nail groove for 48 hours; repeat if necessary.

If hemmorrhage is profuse, dress wound with gauze saturated with Lumicain and allow to remain for 24 hours or longer.

WARNINGS AND PRECAUTIONS

CAUTION: Federal Law restricts sale and use to physician or licensed practitioner.

PACKAGE LABEL

premier lumicainTM Topical Hemostatic Solution 60cc

For Rapid Control of Minor Hemorrhage

Each Gram Contains: Aluminium Chloride............250 mg.

In an aqueous base.

Enter section text here